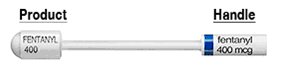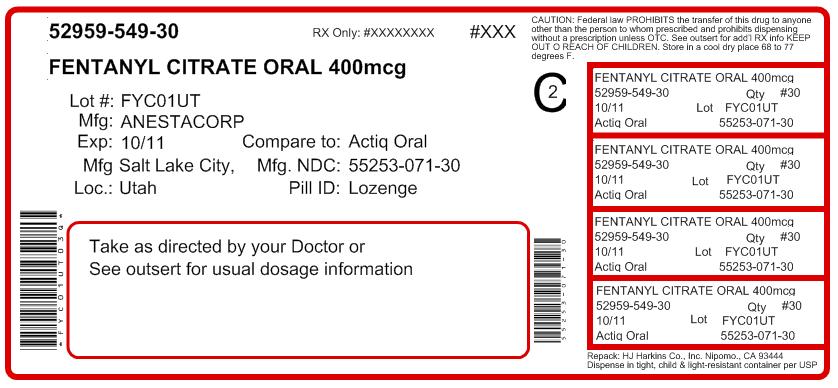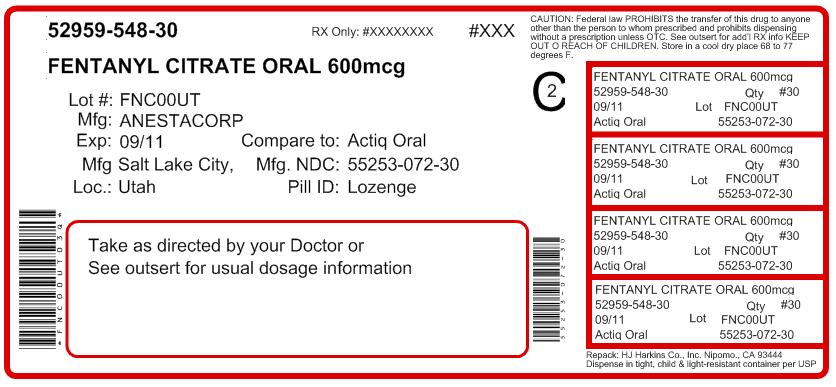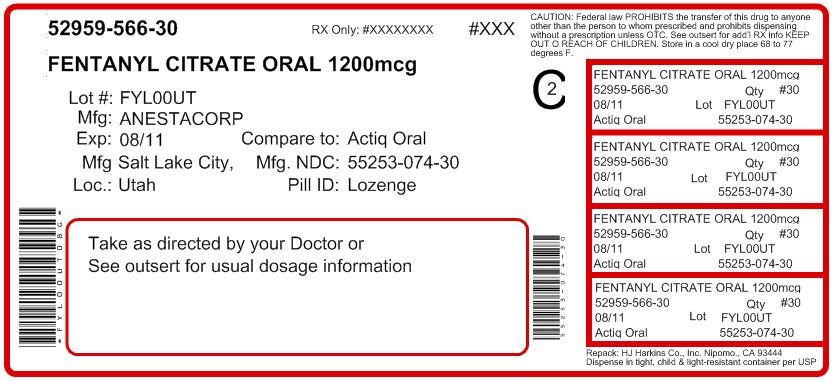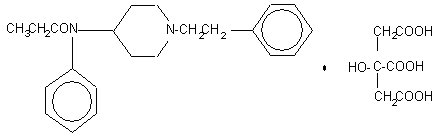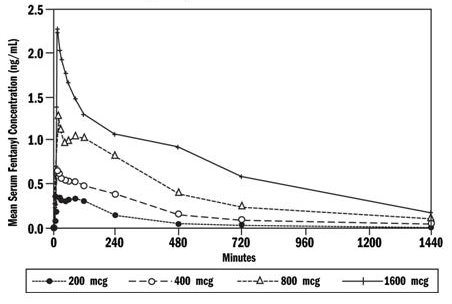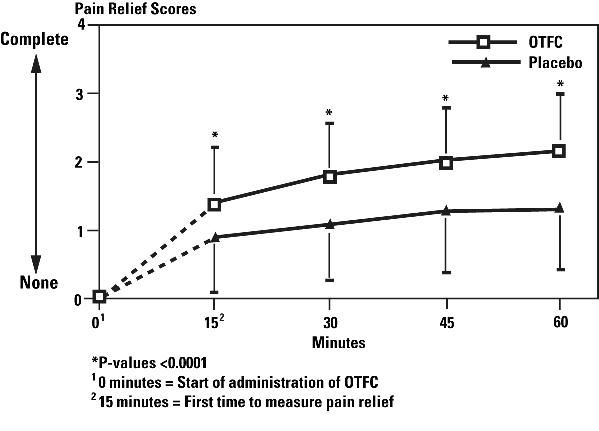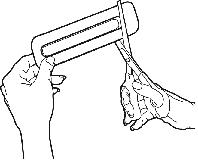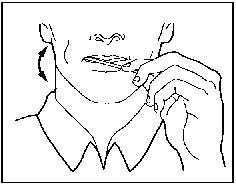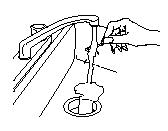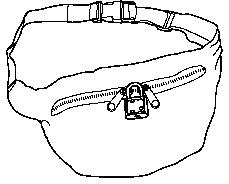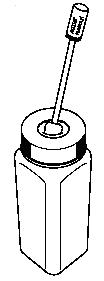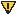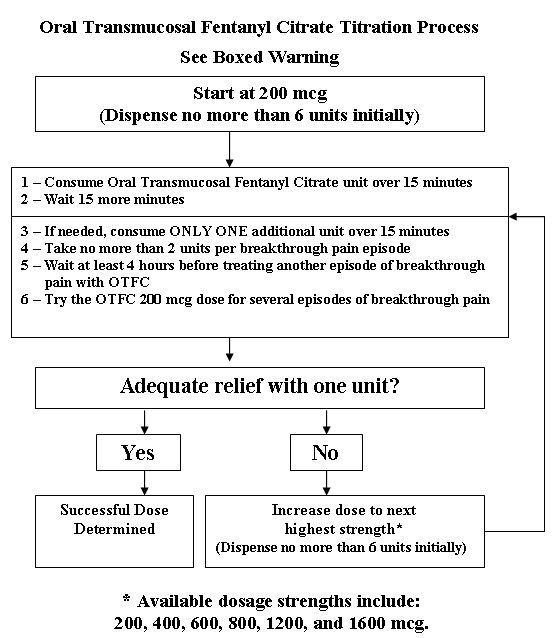 DRUG LABEL: Transmucosal Fentanyl Citrate
NDC: 52959-549 | Form: LOZENGE
Manufacturer: H.J. Harkins Company, Inc.
Category: prescription | Type: HUMAN PRESCRIPTION DRUG LABEL
Date: 20110906
DEA Schedule: CII

ACTIVE INGREDIENTS: FENTANYL CITRATE 400 ug/1 1
INACTIVE INGREDIENTS: DEXTRATES; CITRIC ACID; SODIUM PHOSPHATE, DIBASIC; MAGNESIUM STEARATE; MODIFIED CORN STARCH (1-OCTENYL SUCCINIC ANHYDRIDE); SUCROSE

HIGHLIGHTS OF PRESCRIBING INFORMATION

These highlights do not include all the information needed to use Oral Transmucosal Fentanyl Citrate (OTFC) safely and effectively. See full prescribing information for OTFC.
Oral Transmucosal Fentanyl Citrate (OTFC) (fentanyl citrate) oral transmucosal lozenge, CII
Initial U.S. Approval: 1968

WARNING: IMPORTANCE OF PROPER PATIENT SELECTION and POTENTIAL FOR ABUSE

WARNINGS: IMPORTANCE OF PROPER PATIENT SELECTION and POTENTIAL FOR ABUSE

See full prescribing information for complete boxed warning.

- Must not be used in opioid non-tolerant patients. (1)
- Life-threatening hypoventilation could occur at any dose in patients not taking chronic opiates. (5.2)
- Contraindicated in management of acute or postoperative pain including headache/migraines. (4)
- Contains fentanyl, a Schedule II controlled substance with abuse liability similar to other opioid analgesics. (9.1)
- Contains medicine in an amount that can be fatal to a child. Keep out of reach of children and discard opened units properly. (5.3)
- Use with strong and moderate CYP450 3A4 inhibitors may result in potentially fatal respiratory depression. (7)

RECENT MAJOR CHANGES

Boxed Warning 09/2009

1. INDICATIONS AND USAGE

OTFC is an opioid analgesic indicated only for the management of breakthrough cancer pain in patients 16 and older with malignancies who are already receiving and who are tolerant to around-the-clock opioid therapy for their underlying persistent cancer pain. Patients must remain on around-the-clock opioids when taking OTFC. (1)

2. DOSAGE AND ADMINISTRATION

- Initial dose of OTFC: 200 mcg. Prescribe an initial supply of six 200 mcg OTFC units. (2.1)
- Individually titrate to a tolerable dose that provides adequate analgesia using single OTFC dosage unit per breakthrough cancer pain episode. (2)
- No more than two doses can be taken per breakthrough pain episode. (2.2)
- Wait at least 4 hours before treating another episode of breakthrough pain with OTFC. (2.3)
- Limit consumption to four or fewer units per day once successful dose is found. (2.3)

3. DOSAGE FORMS AND STRENGTHS

- Solid oral transmucosal lozenge in 200 mcg, 400 mcg, 600 mcg, 800 mcg, 1200 mcg and 1600 mcg. (3)

4. CONTRAINDICATIONS

- Opioid non-tolerant patients. (4)
- Management of acute or postoperative pain including headache/migraines. (4)
- Intolerance or hypersensitivity to fentanyl, OTFC, or its components. (4)

5. WARNINGS AND PRECAUTIONS

- Clinically significant respiratory and CNS depression can occur. Monitor patients accordingly. (5.2)
- Full and partially consumed OTFC units contain medicine that can be fatal to a child. Ensure proper storage and disposal. Interim safe storage container available (“OTFC Child Safety Kit”) (5.3)
- Use with other CNS depressants and potent cytochrome P450 3A4 inhibitors may increase depressant effects including respiratory depression, hypotension, and profound sedation. Consider dosage adjustments if warranted. (5.4)
- Titrate OTFC cautiously in patients with chronic obstructive pulmonary disease or preexisting medical conditions predisposing them to respiratory depression. (5.6)
- Administer OTFC with extreme caution in patients susceptible to intracranial effects of CO2 retention. (5.7)

6. ADVERSE REACTIONS

Most common adverse reactions during titration phase (frequency ≥5%): nausea, dizziness, somnolence, vomiting, asthenia, and headache. (6.1)

Most common adverse reactions during treatment (frequency ≥5%): dyspnea, constipation, anxiety, confusion, depression, rash, and insomnia. (6.1)

To report SUSPECTED ADVERSE REACTIONS, contact Cephalon, Inc., at 1-800-896-5855 or FDA at 1-800-FDA-1088 or www.fda.gov/medwatch.

7. DRUG INTERACTIONS

- Monitor patients who begin or end therapy with potent inhibitors of CYP450 3A4 for signs of opioid toxicity. (5.4, 7)

8. USE IN SPECIFIC POPULATIONS

- Safety and efficacy below age 16 years have not been established. (8.4)
- Administer OTFC with caution to patients with liver or kidney dysfunction. (8.6)

FULL PRESCRIBING INFORMATION

WARNING: IMPORTANCE OF PROPER PATIENT SELECTION and POTENTIAL FOR ABUSE

Reports of serious adverse events, including deaths in patients treated with OTFC have been reported. Deaths occurred as a result of improper patient selection (e.g., use in opioid non-tolerant patients) and/or improper dosing. The substitution of OTFC for any other fentanyl product may result in fatal overdose.

OTFC is indicated only for the management of breakthrough cancer pain in patients with malignancies who are already receiving and who are tolerant to around-the-clock opioid therapy for their underlying persistent cancer pain. Patients considered opioid tolerant are those who are taking around-the-clock medicine consisting of at least 60 mg of oral morphine daily, at least 25 mcg of transdermal fentanyl/hour, at least 30 mg of oral oxycodone daily, at least 8 mg oral hydromorphone daily or an equianalgesic dose of another opioid for a week or longer.

OTFC is not indicated for use in opioid non-tolerant patients including those with only as needed (PRN) prior exposure.

Life-threatening respiratory depression could occur at any dose in opioid non-tolerant patients. Deaths have occurred in opioid non-tolerant patients

OTFC is contraindicated in the management of acute or postoperative pain including headache/migraine.

When prescribing, do not convert patients on a mcg per mcg basis to OTFC from other fentanyl products.

When dispensing, do not substitute an OTFC prescription for other fentanyl products. Substantial differences exist in the pharmacokinetic profile of OTFC compared to other fentanyl products that result in clinically important differences in the extent of absorption of fentanyl. As a result of these differences, the substitution of OTFC for any other fentanyl product may result in fatal overdose.

Special care must be used when dosing OTFC. If the breakthrough pain episode is not relieved 15 minutes after completion of the OTFC unit, patients may take ONLY ONE additional dose using the same strength and then must wait at least 4 hours before taking another dose [see Dosage And Administration (2.2)].

OTFC contains fentanyl, an opioid agonist and a Schedule II controlled substance, with an abuse liability similar to other opioid analgesics. OTFC can be abused in a manner similar to other opioid agonists, legal or illicit. This should be considered when prescribing or dispensing OTFC in situations where the physician or pharmacist is concerned about an increased risk of misuse, abuse or diversion. Schedule II opioid substances which include morphine, oxycodone, hydromorphone, oxymorphone, and methadone have the highest potential for abuse and risk of fatal overdose due to respiratory depression

Patients and their caregivers must be instructed that OTFC contains a medicine in an amount which can be fatal to a child. Death has been reported in children who have accidentally ingested OTFC. All units must be kept out of the reach of children and opened units properly discarded. [see Warnings And Precautions (5.3), Patient Counseling Information (17.5, 17.6), and How Supplied/Storage And Handling (16.2)].

OTFC is intended to be used only in the care of cancer patients and only by oncologists and pain specialists who are knowledgeable of and skilled in the use of Schedule II opioids to treat cancer pain.

The concomitant use of OTFC with strong and moderate cytochrome P450 3A4 inhibitors may result in an increase in fentanyl plasma concentrations, and may cause potentially fatal respiratory depression [see Drug Interactions (7)].

1. INDICATIONS AND USAGE

Oral Transmucosal Fentanyl Citrate (OTFC) is indicated only for the management of breakthrough cancer pain in patients 16 and older with malignancies who are already receiving and who are tolerant to around-the-clock opioid therapy for their underlying persistent cancer pain. Patients considered opioid tolerant are those who are taking around-the-clock medicine consisting of at least 60 mg of oral morphine daily, at least 25 mcg of transdermal fentanyl/hour, at least 30 mg of oral oxycodone daily, at least 8 mg of oral hydromorphone daily or an equianalgesic dose of another opioid daily for a week or longer. Patients must remain on around-the-clock opioids when taking OTFC.

This product must not be used in opioid non-tolerant patients because life-threatening respiratory depression and death could occur at any dose in patients not on a chronic regimen of opioids. For this reason, OTFC is contraindicated in the management of acute or postoperative pain.

OTFC is intended to be used only in the care of cancer patients and only by oncologists and pain specialists who are knowledgeable of and skilled in the use of Schedule II opioids to treat cancer pain.

2. DOSAGE AND ADMINISTRATION

As with all opioids, the safety of patients using such products is dependent on health care professionals prescribing them in strict conformity with their approved labeling with respect to patient selection, dosing, and proper conditions for use.

2.1 Initial Dose

Individually titrate OTFC to a dose that provides adequate analgesia and minimizes side effects. The initial dose of OTFC to treat episodes of breakthrough cancer pain is always 200 mcg. The OTFC unit should be consumed over 15 minutes. Patients should be prescribed an initial titration supply of six 200 mcg OTFC units, thus limiting the number of units in the home during titration. Patients should use up all units before increasing to a higher dose to prevent confusion and possible overdose.

2.2 Dose Titration

From this initial dose, closely follow patients and change the dosage level until the patient reaches a dose that provides adequate analgesia using a single OTFC dosage unit per breakthrough cancer pain episode. If signs of excessive opioid effects appear before the unit is consumed, the dosage unit should be removed from the patient’s mouth immediately, disposed of properly, and subsequent doses should be decreased. Patients should record their use of OTFC over several episodes of breakthrough cancer pain and review their experience with their physicians to determine if a dosage adjustment is warranted.

In cases where the breakthrough pain episode is not relieved 15 minutes after completion of the OTFC unit (30 minutes after the start of the unit), patients may take ONLY ONE additional dose of the same strength for that episode. Thus, patients should take a maximum of two doses of OTFC for any breakthrough pain episode.

Patients must wait at least 4 hours before treating another episode of breakthrough pain with OTFC. To reduce the risk of overdosing during titration, patients should have only one strength of OTFC available at any one time.

2.3 Maintenance Dosing

Once titrated to an effective dose, patients should generally use ONLY ONE OTFC unit of the appropriate strength per breakthrough pain episode.

On those occasions when the breakthrough pain episode is not relieved 15 minutes after completion of the OTFC unit, patient may take ONLY ONE additional dose using the same strength for that episode.

Patients MUST wait at least 4 hours before treating another episode of breakthrough pain with OTFC. Once a successful dose has been found (i.e., an average episode is treated with a single unit), patients should limit consumption to four or fewer units per day.

Dosage adjustment of OTFC may be required in some patients in order to continue to provide adequate relief of breakthrough pain.

Generally, the OTFC dose should be increased only when a single administration of the current dose fails to adequately treat the breakthrough pain episode for several consecutive episodes.

If the patient experiences greater than four breakthrough pain episodes per day, the dose of the maintenance (around-the-clock) opioid used for persistent pain should be re-evaluated.

2.4 Administration of OTFC

Open the blister package with scissors immediately prior to product use. The patient should place the OTFC unit in his or her mouth between the cheek and lower gum, occasionally moving the drug matrix from one side to the other using the handle. The OTFC unit should be sucked, not chewed. A unit dose of OTFC, if chewed and swallowed, might result in lower peak concentrations and lower bioavailability than when consumed as directed [see Clinical Pharmacology (12.3)].

The OTFC unit should be consumed over a 15-minute period. Longer or shorter consumption times may produce less efficacy than reported in OTFC clinical trials. If signs of excessive opioid effects appear before the unit is consumed, remove the drug matrix from the patient’s mouth immediately and decrease future doses.

2.5 Discontinuation of OTFC

For patients requiring discontinuation of opioids, a gradual downward titration is recommended because it is not known at what dose level the opioid may be discontinued without producing the signs and symptoms of abrupt withdrawal.

3. DOSAGE FORMS AND STRENGTHS

Each dosage unit has white to off-white color and is a solid drug matrix on a handle. Each strength is marked on the individual solid drug matrix and the handle tag. OTFC is available in 200 mcg, 400 mcg, 600 mcg, 800 mcg, 1200 mcg and 1600 mcg strengths [see How Supplied/Storage And Handling (16.3)].

4. CONTRAINDICATIONS

OTFC is contraindicated in opioid non-tolerant patients. OTFC is contraindicated in the management of acute or postoperative pain including headache/migraine. Life-threatening respiratory depression and death could occur at any dose in opioid non-tolerant patients.

Patients considered opioid tolerant are those who are taking around-the-clock medicine consisting of at least 60 mg of oral morphine daily, at least 25 mcg of transdermal fentanyl/hour, at least 30 mg of oral oxycodone daily, at least 8 mg of oral hydromorphone daily, or an equianalgesic dose of another opioid daily for a week or longer.

OTFC is contraindicated in patients with known intolerance or hypersensitivity to any of its components or the drug fentanyl. Anaphylaxis and hypersensitivity have been reported in association with the use of OTFC.

5. WARNINGS AND PRECAUTIONS

See Boxed Warning - WARNING: IMPORTANCE OF PROPER PATIENT SELECTION, DOSING, and POTENTIAL FOR ABUSE

5.1 Important Information Regarding Prescribing and Dispensing

When prescribing, DO NOT convert a patient to OTFC from any other fentanyl product on a mcg per mcg basis as OTFC and other fentanyl products are not equivalent on a microgram per microgram basis.

OTFC is NOT a generic version of Fentora®. When dispensing, DO NOT substitute an OTFC prescription for a Fentora prescription under any circumstances. Fentora and OTFC are not equivalent. Substantial differences exist in the pharmacokinetic profile of OTFC compared to other fentanyl products including Fentora that result in clinically important differences in the rate and extent of absorption of fentanyl. As a result of these differences, the substitution of OTFC for any other fentanyl product may result in a fatal overdose.

There are no safe conversion directions available for patients on any other fentanyl products. (Note: This includes oral, transdermal, or parenteral formulations of fentanyl.) Therefore, for opioid tolerant patients, the initial dose of OTFC should always be 200 mcg. Each patient should be individually titrated to provide adequate analgesia while minimizing side effects [see Dosage And Administration (2.2)].

5.2 Respiratory Depression

As with all opioids, there is a risk of clinically significant respiratory depression in patients using OTFC. Accordingly, follow all patients for symptoms of respiratory depression. Respiratory depression may occur more readily when opioids are given in conjunction with other agents that depress respiration.

5.3 Patient/Caregiver Instructions

Patients and their caregivers must be instructed that OTFC contains a medicine in an amount which can be fatal to a child. Death has been reported in children who have accidentally ingested OTFC. Patients and their caregivers must be instructed to keep both used and unused dosage units out of the reach of children. While all units should be disposed of immediately after use, partially consumed units represent a special risk to children. In the event that a unit is not completely consumed it must be properly disposed as soon as possible [see How Supplied/Storage And Handling (16.1, 16.2), and Patient Counseling Information (17.1) and the Medication Guide].

Physicians and dispensing pharmacists must specifically question patients or caregivers about the presence of children in the home (on a full time or visiting basis) and counsel them regarding the dangers to children from inadvertent exposure.

OTFC could be fatal to individuals for whom it is not prescribed and for those who are not opioid-tolerant.

5.4 Additive CNS Depressant Effects

The concomitant use of OTFC with other CNS depressants, including other opioids, sedatives or hypnotics, general anesthetics, phenothiazines, tranquilizers, skeletal muscle relaxants, sedating antihistamines, and alcoholic beverages may produce increased depressant effects (e.g., respiratory depression, hypotension, and profound sedation). Concomitant use with potent inhibitors of cytochrome P450 3A4 isoform (e.g., erythromycin, ketoconazole, and certain protease inhibitors) may increase fentanyl levels, resulting in increased depressant effects [see Drug Interactions (7)].

Patients on concomitant CNS depressants must be monitored for a change in opioid effects. Consideration should be given to adjusting the dose of OTFC if warranted.

5.5 Effects on Ability to Drive and Use Machines

Opioid analgesics impair the mental and/or physical ability required for the performance of potentially dangerous tasks (e.g., driving a car or operating machinery). Warn patients taking OTFC of these dangers and counsel them accordingly.

5.6 Chronic Pulmonary Disease

Because potent opioids can cause respiratory depression, titrate OTFC with caution in patients with chronic obstructive pulmonary disease or preexisting medical conditions predisposing them to respiratory depression. In such patients, even normal therapeutic doses of OTFC may further decrease respiratory drive to the point of respiratory failure.

5.7 Head Injuries and Increased Intracranial Pressure

Administer OTFC with extreme caution in patients who may be particularly susceptible to the intracranial effects of CO2 retention such as those with evidence of increased intracranial pressure or impaired consciousness. Opioids may obscure the clinical course of a patient with a head injury and should be used only if clinically warranted.

5.8 Cardiac Disease

Intravenous fentanyl may produce bradycardia. Therefore, use OTFC with caution in patients with bradyarrhythmias.

5.9 MAO Inhibitors

OTFC is not recommended for use in patients who have received MAO inhibitors within 14 days, because severe and unpredictable potentiation by MAO inhibitors has been reported with opioid analgesics.

6. ADVERSE REACTIONS

6.1 Clinical Studies Experience

The safety of OTFC (oral transmucosal fentanyl citrate) has been evaluated in 257 opioid-tolerant chronic cancer pain patients. The duration of OTFC use varied during the open-label study. Some patients were followed for over 21 months. The average duration of therapy in the open-label study was 129 days.

The adverse reactions seen with OTFC are typical opioid side effects. Frequently, these adverse reactions will cease or decrease in intensity with continued use of OTFC, as the patient is titrated to the proper dose. Expect opioid side effects and manage them accordingly.

The most serious adverse reactions associated with all opioids including OTFC are respiratory depression (potentially leading to apnea or respiratory arrest), circulatory depression, hypotension, and shock. Follow all patients for symptoms of respiratory depression.

Because the clinical trials of OTFC were designed to evaluate safety and efficacy in treating breakthrough cancer pain, all patients were also taking concomitant opioids, such as sustained-release morphine or transdermal fentanyl, for their persistent cancer pain. The adverse event data presented here reflect the actual percentage of patients experiencing each adverse effect among patients who received OTFC for breakthrough cancer pain along with a concomitant opioid for persistent cancer pain. There has been no attempt to correct for concomitant use of other opioids, duration of OTFC therapy, or cancer-related symptoms. Adverse reactions are included regardless of causality or severity.

Because clinical trials are conducted under widely varying conditions, adverse reaction rates observed in the clinical trials of a drug cannot be directly compared to rates in the clinical trials of another drug and may not reflect the rates observed in practice.

Three short-term clinical trials with similar titration schemes were conducted in 257 patients with malignancy and breakthrough cancer pain. Data are available for 254 of these patients. The goal of titration in these trials was to find the dose of OTFC that provided adequate analgesia with acceptable side effects (successful dose). Patients were titrated from a low dose to a successful dose in a manner similar to current titration dosing guidelines. Table 1 lists, by dose groups, adverse reactions with an overall frequency of 1% or greater that occurred during titration and are commonly associated with opioid administration or are of particular clinical interest. The ability to assign a dose-response relationship to these adverse reactions is limited by the titration schemes used in these studies. Adverse reactions are listed in descending order of frequency within each body system.

Table 1. Percent of Patients with Specific Adverse Events Commonly Associated with Opioid Administration or of Particular Clinical Interest Which Occurred During Titration (Events in 1% or More of Patients)
Dose Group |  | Percentage of Patients Reporting Event
Dose Group |  | 200-600 mcg | 800-1400 mcg | 1600 mcg | >1600 mcg | Any Dose*
Dose Group |  | (n=230) | (n=138) | (n=54) | (n=41) | (n=254)
Body As A Whole
 | Asthenia | 6 | 4 | 0 | 7 | 9
 | Headache | 3 | 4 | 6 | 5 | 6
 | Accidental Injury | 1 | 1 | 4 | 0 | 2
Digestive
 | Nausea | 14 | 15 | 11 | 22 | 23
 | Vomiting | 7 | 6 | 6 | 15 | 12
 | Constipation | 1 | 4 | 2 | 0 | 4
Nervous
 | Dizziness | 10 | 16 | 6 | 15 | 17
 | Somnolence | 9 | 9 | 11 | 20 | 17
 | Confusion | 1 | 6 | 2 | 0 | 4
 | Anxiety | 3 | 0 | 2 | 0 | 3
 | Abnormal Gait | 0 | 1 | 4 | 0 | 2
 | Dry Mouth | 1 | 1 | 2 | 0 | 2
 | Nervousness | 1 | 1 | 0 | 0 | 2
 | Vasodilatation | 2 | 0 | 2 | 0 | 2
 | Hallucinations | 0 | 1 | 2 | 2 | 1
 | Insomnia | 0 | 1 | 2 | 0 | 1
 | Thinking Abnormal | 0 | 1 | 2 | 0 | 1
 | Vertigo | 1 | 0 | 0 | 0 | 1
Respiratory
 | Dyspnea | 2 | 3 | 6 | 5 | 4
Skin
 | Pruritus | 1 | 0 | 0 | 5 | 2
 | Rash | 1 | 1 | 0 | 2 | 2
 | Sweating | 1 | 1 | 2 | 2 | 2
Special Senses
 | Abnormal Vision | 1 | 0 | 2 | 0 | 2
* Any Dose = A patient who experienced the same adverse event at multiple doses was only counted once

The following adverse reactions not reflected in Table 1 occurred during titration with an overall frequency of 1% or greater and are listed in descending order of frequency within each body system.

Body as a Whole: Pain, fever, abdominal pain, chills, back pain, chest pain, infection

Cardiovascular: Migraine

Digestive: Diarrhea, dyspepsia, flatulence

Metabolic and Nutritional: Peripheral edema, dehydration

Nervous: Hypesthesia

Respiratory: Pharyngitis, cough increased

The following reactions occurred during titration with an overall frequency of less than 1% and are listed in descending order of frequency within each body system.

Body as a Whole: Flu syndrome, abscess, bone pain

Cardiovascular: Deep thrombophlebitis, hypertension, hypotension

Digestive: Anorexia, eructation, esophageal stenosis, fecal impaction, gum hemorrhage, mouth ulceration, oral moniliasis

Hemic and Lymphatic: Anemia, leukopenia

Metabolic and Nutritional: Edema, hypercalcemia, weight loss

Musculoskeletal: Myalgia, pathological fracture, myasthenia

Nervous: Abnormal dreams, urinary retention, agitation, amnesia, emotional lability, euphoria, incoordination, libido decreased, neuropathy, paresthesia, speech disorder

Respiratory: Hemoptysis, pleural effusion, rhinitis, asthma, hiccup, pneumonia, respiratory insufficiency, sputum increased

Skin and Appendages: Alopecia, exfoliative dermatitis

Special Senses: Taste perversion

Urogenital: Vaginal hemorrhage, dysuria, hematuria, urinary incontinence, urinary tract infection

A long-term extension study was conducted in 156 patients with malignancy and breakthrough cancer pain who were treated for an average of 129 days. Data are available for 152 of these patients. Table 2 lists by dose groups, adverse reactions with an overall frequency of 1% or greater that occurred during the long-term extension study and are commonly associated with opioid administration or are of particular clinical interest. Adverse reactions are listed in descending order of frequency within each body system.

Table 2. Percent of Patients with Adverse Events Commonly Associated with Opioid Administration or of Particular Clinical Interest Which Occurred During Long Term Treatment (Events in 1% or More of Patients)
Dose Group |  | Percentage of Patients Reporting Event
Dose Group |  | 200-600 mcg | 800-1400 mcg | 1600 mcg | >1600 mcg | Any Dose*
Dose Group |  | (n=98) | (n=83) | (n=53) | (n=27) | (n=152)
Body As A Whole
 | Asthenia | 25 | 30 | 17 | 15 | 38
 | Headache | 12 | 17 | 13 | 4 | 20
 | Accidental Injury | 4 | 6 | 4 | 7 | 9
 | Hypertonia | 2 | 2 | 2 | 0 | 3
Digestive
 | Nausea | 31 | 36 | 25 | 26 | 45
 | Vomiting | 21 | 28 | 15 | 7 | 31
 | Constipation | 14 | 11 | 13 | 4 | 20
 | Intestinal Obstruction | 0 | 2 | 4 | 0 | 3
Cardiovascular
 | Hypertension | 1 | 1 | 0 | 0 | 1
Nervous
 | Dizziness | 12 | 10 | 9 | 0 | 16
 | Anxiety | 9 | 8 | 8 | 7 | 15
 | Somnolence | 8 | 13 | 8 | 7 | 15
 | Confusion | 2 | 5 | 13 | 7 | 10
 | Depression | 9 | 4 | 2 | 7 | 9
 | Insomnia | 5 | 1 | 8 | 4 | 7
 | Abnormal Gait | 5 | 1 | 0 | 0 | 4
 | Dry Mouth | 3 | 1 | 2 | 4 | 4
 | Nervousness | 2 | 2 | 0 | 4 | 3
 | Stupor | 4 | 1 | 0 | 0 | 3
 | Vasodilatation | 1 | 1 | 4 | 0 | 3
 | Thinking Abnormal | 2 | 1 | 0 | 0 | 2
 | Abnormal Dreams | 1 | 1 | 0 | 0 | 1
 | Convulsion | 0 | 1 | 2 | 0 | 1
 | Myoclonus | 0 | 0 | 4 | 0 | 1
 | Tremor | 0 | 1 | 2 | 0 | 1
 | Vertigo | 0 | 0 | 4 | 0 | 1
Respiratory
 | Dyspnea | 15 | 16 | 8 | 7 | 22
Skin
 | Rash | 3 | 5 | 8 | 4 | 8
 | Sweating | 3 | 2 | 2 | 0 | 4
 | Pruritus | 2 | 0 | 2 | 0 | 2
Special Senses
 | Abnormal Vision | 2 | 2 | 0 | 0 | 3
Urogenital
 | Urinary Retention | 1 | 2 | 0 | 0 | 2

The following reactions not reflected in Table 2 occurred with an overall frequency of 1% or greater in the long-term extension study and are listed in descending order of frequency within each body system.

Body as a Whole: Pain, fever, back pain, abdominal pain, chest pain, flu syndrome, chills, infection, abdomen enlarged, bone pain, ascites, sepsis, neck pain, viral infection, fungal infection, cachexia, cellulitis, malaise, pelvic pain

Cardiovascular: Deep thrombophlebitis, migraine, palpitation, vascular disorder

Digestive: Diarrhea, anorexia, dyspepsia, dysphagia, oral moniliasis, mouth ulceration, rectal disorder, stomatitis, flatulence, gastrointestinal hemorrhage, gingivitis, jaundice, periodontal abscess, eructation, glossitis, rectal hemorrhage

Hemic and Lymphatic: Anemia, leukopenia, thrombocytopenia, ecchymosis, lymphadenopathy, lymphedema, pancytopenia

Metabolic and Nutritional: Peripheral edema, edema, dehydration, weight loss, hyperglycemia, hypokalemia, hypercalcemia, hypomagnesemia

Musculoskeletal: Myalgia, pathological fracture, joint disorder, leg cramps, arthralgia, bone disorder

Nervous: Hypesthesia, paresthesia, hypokinesia, neuropathy, speech disorder

Respiratory: Cough increased, pharyngitis, pneumonia, rhinitis, sinusitis, bronchitis, epistaxis, asthma, hemoptysis, sputum increased

Skin and Appendages: Skin ulcer, alopecia

Special Senses: Tinnitus, conjunctivitis, ear disorder, taste perversion

Urogenital: Urinary tract infection, urinary incontinence, breast pain, dysuria, hematuria, scrotal edema, hydronephrosis, kidney failure, urinary urgency, urination impaired, breast neoplasm, vaginal hemorrhage, vaginitis

The following reactions occurred with a frequency of less than 1% in the long-term extension study and are listed in descending order of frequency within each body system.

Body as a Whole: Allergic reaction, cyst, face edema, flank pain, granuloma, bacterial infection, injection site pain, mucous membrane disorder, neck rigidity

Cardiovascular: Angina pectoris, hemorrhage, hypotension, peripheral vascular disorder, postural hypotension, tachycardia

Digestive: Cheilitis, esophagitis, fecal incontinence, gastroenteritis, gastrointestinal disorder, gum hemorrhage, hemorrhage of colon, hepatorenal syndrome, liver tenderness, tooth caries, tooth disorder

Hemic and Lymphatic: Bleeding time increased

Metabolic and Nutritional: Acidosis, generalized edema, hypocalcemia, hypoglycemia, hyponatremia, hypoproteinemia, thirst

Musculoskeletal: Arthritis, muscle atrophy, myopathy, synovitis, tendon disorder

Nervous: Acute brain syndrome, agitation, cerebral ischemia, facial paralysis, foot drop, hallucinations, hemiplegia, miosis, subdural hematoma

Respiratory: Hiccup, hyperventilation, lung disorder, pneumothorax, respiratory failure, voice alteration

Skin and Appendages: Herpes zoster, maculopapular rash, skin discoloration, urticaria, vesiculobullous rash

Special Senses: Ear pain, eye hemorrhage, lacrimation disorder, partial permanent deafness, partial transitory deafness

Urogenital: Kidney pain, nocturia, oliguria, polyuria, pyelonephritis

6.2 Post-Marketing Experience

Adverse reactions are reported voluntarily from a population of uncertain size, and, therefore, it is not always possible to reliably estimate their frequency or establish a causal relationship to drug exposure. Decisions to include these reactions in labeling are typically based on one or more of the following factors: (1) seriousness of the reaction, (2) frequency of the reporting, or (3) strength of causal connection to OTFC.

The following adverse reactions have been identified during postapproval use of OTFC (which contains approximately 2 grams of sugar per unit):

Digestive: Dental decay of varying severity including dental caries, tooth loss, and gum line erosion.

General Disorders and Administration Site Conditions: Application site reactions including irritation, pain, and ulcer.

7. DRUG INTERACTIONS

Fentanyl is metabolized mainly via the human cytochrome P450 3A4 isoenzyme system (CYP3A4); therefore potential interactions may occur when OTFC is given concurrently with agents that affect CYP3A4 activity. The concomitant use of OTFC with strong CYP3A4 inhibitors (e.g., ritonavir, ketoconazole, itraconazole, troleandomycin, clarithromycin, nelfinavir, and nefazodone) or moderate CYP3A4 inhibitors (e.g., amprenavir, aprepitant, diltiazem, erythromycin, fluconazole, fosamprenavir, and verapamil) may result in increased fentanyl plasma concentrations, potentially causing serious adverse drug effects including fatal respiratory depression. Patients receiving OTFC concomitantly with moderate or strong CYP3A4 inhibitors should be carefully monitored for an extended period of time. Dosage increase should be done conservatively.

Grapefruit and grapefruit juice decrease CYP3A4 activity, increasing blood concentrations of fentanyl, thus should be avoided.

Drugs that induce cytochrome P450 3A4 activity may have the opposite effects.

Concomitant use of OTFC with an MAO inhibitor, or within 14 days of discontinuation, is not recommended [see Warnings And Precautions (5.9)].

8. USE IN SPECIFIC POPULATIONS

8.1 Pregnancy

Pregnancy Category C

There are no adequate and well-controlled studies in pregnant women. OTFC should be used during pregnancy only if the potential benefit justifies the potential risk to the fetus.No epidemiological studies of congenital anomalies in infants born to women treated with fentanyl during pregnancy have been reported.

Chronic maternal treatment with fentanyl during pregnancy has been associated with transient respiratory depression, behavioral changes, or seizures in newborn infants characteristic of neonatal abstinence syndrome.

In women treated acutely with intravenous or epidural fentanyl during labor, symptoms of neonatal respiratory or neurological depression were no more frequent than would be expected in infants of untreated mothers.

Transient neonatal muscular rigidity has been observed in infants whose mothers were treated with intravenous fentanyl.

Fentanyl is embryocidal in rats as evidenced by increased resorptions in pregnant rats at doses of 30 mcg/kg IV or 160 mcg/kg SC. Conversion to human equivalent doses indicates this is within the range of the human recommended dosing for OTFC.

Fentanyl citrate was not teratogenic when administered to pregnant animals. Published studies demonstrated that administration of fentanyl (10, 100, or 500 mcg/kg/day) to pregnant rats from day 7 to 21, of their 21 day gestation, via implanted microosmotic minipumps was not teratogenic (the high dose was approximately 3-times the human dose of 1600 mcg per pain episode on a mg/m^2 basis). Intravenous administration of fentanyl (10 or 30 mcg/kg) to pregnant female rats from gestation day 6 to 18, was embryo or fetal toxic, and caused a slightly increased mean delivery time in the 30 mcg/kg/day group, but was not teratogenic.

8.2 Labor and Delivery

Fentanyl readily passes across the placenta to the fetus; therefore do not use OTFC during labor and delivery.

8.3 Nursing Mothers

Fentanyl is excreted in human milk; therefore, do not use OTFC in nursing women because of the possibility of sedation and/or respiratory depression in their infants. Symptoms of opioid withdrawal may occur in infants at the cessation of nursing by women using OTFC.

8.4 Pediatric Use

Safety and effectiveness in pediatric patients below 16 years of age have not been established.

In a clinical study, 15 opioid-tolerant pediatric patients with breakthrough pain, ranging in age from 5 to 15 years, were treated with OTFC. The study was too small to allow conclusions on safety and efficacy in this patient population. Twelve of the fifteen opioid-tolerant children and adolescents aged 5 to 15 years in this study received OTFC at doses ranging from 200 mcg to 600 mcg. The mean (CV%; range) dose-normalized (to 200 mcg) Cmax and AUC0-8 values were 0.87 ng/mL (51%; 0.42-1.30) and 4.54 ng×h/mL (42%; 2.37-6.0), respectively, for children ages 5 to <11 years old (N = 3) and 0.68 ng/mL (72%; 0.15-1.44) and 8.38 (192%; 0.84-50.78), respectively, for children ages ≥11 to <16 y (N = 9).

8.5 Geriatric Use

Of the 257 patients in clinical studies of OTFC in breakthrough cancer pain, 61 (24%) were 65 years of age and older, while 15 (6%) were 75 years of age and older. Those patients over the age of 65 years were titrated to a mean dose that was about 200 mcg less than the mean dose titrated to by younger patients. No difference was noted in the safety profile of the group over 65 years of age as compared to younger patients in OTFC clinical trials.

Elderly patients have been shown to be more sensitive to the effects of fentanyl when administered intravenously, compared with the younger population. Therefore, exercise caution when individually titrating OTFC in elderly patients to provide adequate efficacy while minimizing risk.

8.6 Patients with Renal or Hepatic Impairment

Insufficient information exists to make recommendations regarding the use of OTFC in patients with impaired renal or hepatic function. Fentanyl is metabolized primarily via human cytochrome P450 3A4 isoenzyme system and mostly eliminated in urine. If the drug is used in these patients, it should be used with caution because of the hepatic metabolism and renal excretion of fentanyl.

8.7 Gender

Both male and female opioid-tolerant cancer patients were studied for the treatment of breakthrough cancer pain. No clinically relevant gender differences were noted either in dosage requirement or in observed adverse reactions.

9. DRUG ABUSE AND DEPENDENCE

9.1 Controlled Substance

Fentanyl is a Schedule II controlled substance that can produce drug dependence of the morphine type. OTFC may be subject to misuse, abuse and addiction.

9.2 Abuse and Addiction

Manage the handling of OTFC to minimize the risk of diversion, including restriction of access and accounting procedures as appropriate to the clinical setting and as required by law [see How Supplied/Storage And Handling (16.1, 16.2)].

Concerns about abuse, addiction, and diversion should not prevent the proper management of pain. However, all patients treated with opioids require careful monitoring for signs of abuse and addiction, because use of opioid analgesic products carries the risk of addiction even under appropriate medical use.

Addiction is a primary, chronic, neurobiologic disease, with genetic, psychosocial, and environmental factors influencing its development and manifestations. It is characterized by behaviors that include one or more of the following: impaired control over drug use, compulsive use, continued use despite harm, and craving. Drug addiction is a treatable disease, utilizing a multidisciplinary approach, but relapse is common. "Drug-seeking" behavior is very common in addicts and drug abusers.

Abuse and addiction are separate and distinct from physical dependence and tolerance. Physicians should be aware that addiction may not be accompanied by concurrent tolerance and symptoms of physical dependence in all addicts. In addition, abuse of opioids can occur in the absence of addiction and is characterized by misuse for nonmedical purposes, often in combination with other psychoactive substances. Since OTFC may be diverted for non-medical use, careful record keeping of prescribing information, including quantity, frequency, and renewal requests is strongly advised.

Proper assessment of patients, proper prescribing practices, periodic re-evaluation of therapy, and proper dispensing and storage are appropriate measures that help to limit abuse of opioid drugs.

Healthcare professionals should contact their State Professional Licensing Board, or State Controlled Substances Authority for information on how to prevent and detect abuse or diversion of this product.

9.3 Dependence

Guide the administration of OTFC by the response of the patient. Physical dependence, per se, is not ordinarily a concern when one is treating a patient with chronic cancer pain, and fear of tolerance and physical dependence should not deter using doses that adequately relieve the pain.

Opioid analgesics may cause physical dependence. Physical dependence results in withdrawal symptoms in patients who abruptly discontinue the drug. Withdrawal also may be precipitated through the administration of drugs with opioid antagonist activity, e.g., naloxone, nalmefene, or mixed agonist/antagonist analgesics (pentazocine, butorphanol, buprenorphine, nalbuphine).

Physical dependence usually does not occur to a clinically significant degree until after several weeks of continued opioid usage. Tolerance, in which increasingly larger doses are required in order to produce the same degree of analgesia, is initially manifested by a shortened duration of analgesic effect, and subsequently, by decreases in the intensity of analgesia.

10. OVERDOSAGE

10.1 Clinical Presentation

The manifestations of OTFC overdosage are expected to be similar in nature to intravenous fentanyl and other opioids, and are an extension of its pharmacological actions with the most serious significant effect being respiratory depression [see Clinical Pharmacology (12.2)].

10.2 Immediate Management

Immediate management of opioid overdose includes removal of the OTFC unit, if still in the mouth, ensuring a patent airway, physical and verbal stimulation of the patient, and assessment of level of consciousness, ventilatory and circulatory status.

10.3 Treatment of Overdosage (Accidental Ingestion) in the Opioid NON-Tolerant Person

Provide ventilatory support, obtain intravenous access, and employ naloxone or other opioid antagonists as clinically indicated. The duration of respiratory depression following overdose may be longer than the effects of the opioid antagonist’s action (e.g., the half-life of naloxone ranges from 30 to 81 minutes) and repeated administration may be necessary. Consult the package insert of the individual opioid antagonist for details about such use.

10.4 Treatment of Overdose in Opioid-Tolerant Patients

Provide ventilatory support and obtain intravenous access as clinically indicated. Judicious use of naloxone or another opioid antagonist may be warranted in some instances, but it is associated with the risk of precipitating an acute withdrawal syndrome.

10.5 General Considerations for Overdose

Management of severe OTFC overdose includes: securing a patent airway, assisting or controlling ventilation, establishing intravenous access, and GI decontamination by lavage and/or activated charcoal, once the patient's airway is secure. In the presence of respiratory depression or apnea, assist or control ventilation, and administer oxygen as indicated.

Although muscle rigidity interfering with respiration has not been seen following the use of OTFC, this is possible with fentanyl and other opioids. If it occurs, manage it by using assisted or controlled ventilation, by an opioid antagonist, and as a final alternative, by a neuromuscular blocking agent.

11. DESCRIPTION

OTFC (oral transmucosal fentanyl citrate) is a solid formulation of fentanyl citrate, a potent opioid analgesic, intended for oral transmucosal administration. OTFC is formulated as a white to off-white solid drug matrix on a handle that is fracture resistant (ABS plastic) under normal conditions when used as directed.

OTFC is designed to be dissolved slowly in the mouth to facilitate transmucosal absorption. The handle allows the OTFC unit to be removed from the mouth if signs of excessive opioid effects appear during administration.

Active Ingredient: Fentanyl citrate, USP is N-(1-Phenethyl-4-piperidyl) propionanilide citrate (1:1). Fentanyl is a highly lipophilic compound (octanol-water partition coefficient at pH 7.4 is 816:1) that is freely soluble in organic solvents and sparingly soluble in water (1:40). The molecular weight of the free base is 336.5 (the citrate salt is 528.6). The pKa of the tertiary nitrogens are 7.3 and 8.4. The compound has the following structural formula:

Inactive Ingredients: Hydrated dextrates, citric acid, dibasic sodium phosphate, artificial berry flavor, magnesium stearate, and edible glue (modified food starch and confectioner's sugar).

12. CLINICAL PHARMACOLOGY

12.1 Mechanism of Action

Fentanyl is a pure opioid agonist whose principal therapeutic action is analgesia. Other members of the class known as opioid agonists include substances such as morphine, oxycodone, hydromorphone, codeine, and hydrocodone.

12.2 Pharmacodynamics

Pharmacological effects of opioid agonists include anxiolysis, euphoria, feelings of relaxation, respiratory depression, constipation, miosis, cough suppression, and analgesia. Like all pure opioid agonist analgesics, with increasing doses there is increasing analgesia, unlike with mixed agonist/antagonists or non-opioid analgesics, where there is a limit to the analgesic effect with increasing doses. With pure opioid agonist analgesics, there is no defined maximum dose; the ceiling to analgesic effectiveness is imposed only by side effects, the more serious of which may include somnolence and respiratory depression.

Analgesia

The analgesic effects of fentanyl are related to the blood level of the drug, if proper allowance is made for the delay into and out of the CNS (a process with a 3- to 5-minute half-life).

In general, the effective concentration and the concentration at which toxicity occurs increase with increasing tolerance with any and all opioids. The rate of development of tolerance varies widely among individuals. As a result, the dose of OTFC should be individually titrated to achieve the desired effect [see Dosage And Administration (2.2)].

Central Nervous System

The precise mechanism of the analgesic action is unknown although fentanyl is known to be a mu-opioid receptor agonist. Specific CNS opioid receptors for endogenous compounds with opioid-like activity have been identified throughout the brain and spinal cord and play a role in the analgesic effects of this drug.

Fentanyl produces respiratory depression by direct action on brain stem respiratory centers. The respiratory depression involves both a reduction in the responsiveness of the brain stem to increases in carbon dioxide and to electrical stimulation.

Fentanyl depresses the cough reflex by direct effect on the cough center in the medulla. Antitussive effects may occur with doses lower than those usually required for analgesia.

Fentanyl causes miosis even in total darkness. Pinpoint pupils are a sign of opioid overdose but are not pathognomonic (e.g., pontine lesions of hemorrhagic or ischemic origin may produce similar findings).

Gastrointestinal System

Fentanyl causes a reduction in motility associated with an increase in smooth muscle tone in the antrum of the stomach and in the duodenum. Digestion of food is delayed in the small intestine and propulsive contractions are decreased. Propulsive peristaltic waves in the colon are decreased, while tone may be increased to the point of spasm resulting in constipation. Other opioid-induced effects may include a reduction in gastric, biliary and pancreatic secretions, spasm of the sphincter of Oddi, and transient elevations in serum amylase.

Cardiovascular System

Fentanyl may produce release of histamine with or without associated peripheral vasodilation. Manifestations of histamine release and/or peripheral vasodilation may include pruritus, flushing, red eyes, sweating, and/or orthostatic hypotension.

Endocrine System

Opioid agonists have been shown to have a variety of effects on the secretion of hormones. Opioids inhibit the secretion of ACTH, cortisol, and luteinizing hormone (LH) in humans. They also stimulate prolactin, growth hormone (GH) secretion, and pancreatic secretion of insulin and glucagon in humans and other species, rats and dogs. Thyroid stimulating hormone (TSH) has been shown to be both inhibited and stimulated by opioids.

Respiratory System

All opioid mu-receptor agonists, including fentanyl, produce dose-dependent respiratory depression. The risk of respiratory depression is less in patients receiving chronic opioid therapy who develop tolerance to respiratory depression and other opioid effects. During the titration phase of the clinical trials, somnolence, which may be a precursor to respiratory depression, did increase in patients who were treated with higher doses of OTFC. Peak respiratory depressive effects may be seen as early as 15 to 30 minutes from the start of oral transmucosal fentanyl citrate product administration and may persist for several hours.

Serious or fatal respiratory depression can occur even at recommended doses. Fentanyl depresses the cough reflex as a result of its CNS activity. Although not observed with oral transmucosal fentanyl products in clinical trials, fentanyl given rapidly by intravenous injection in large doses may interfere with respiration by causing rigidity in the muscles of respiration. Therefore, physicians and other healthcare providers should be aware of this potential complication [see Boxed Warning - Warning: Importance Of Proper Patient Selection, Dosing, and Potential for Abuse, Contraindications (4), Warnings And Precautions (5.2), Adverse Reactions (6), and Overdosage (10)].

12.3 Pharmacokinetics

Absorbtion

The absorption pharmacokinetics of fentanyl from the oral transmucosal dosage form is a combination of an initial rapid absorption from the buccal mucosa and a more prolonged absorption of swallowed fentanyl from the GI tract. Both the blood fentanyl profile and the bioavailability of fentanyl will vary depending on the fraction of the dose that is absorbed through the oral mucosa and the fraction swallowed.

Absolute bioavailability, as determined by area under the concentration-time curve, of 15 mcg/kg in 12 adult males was 50% compared to intravenous fentanyl.

Normally, approximately 25% of the total dose of OTFC is rapidly absorbed from the buccal mucosa and becomes systemically available. The remaining 75% of the total dose is swallowed with the saliva and then is slowly absorbed from the GI tract. About 1/3 of this amount (25% of the total dose) escapes hepatic and intestinal first-pass elimination and becomes systemically available. Thus, the generally observed 50% bioavailability of OTFC is divided equally between rapid transmucosal and slower GI absorption. Therefore, a unit dose of OTFC, if chewed and swallowed, might result in lower peak concentrations and lower bioavailability than when consumed as directed.

Dose proportionality among four of the available strengths of OTFC (200, 400, 800, and 1600 mcg) has been demonstrated in a balanced crossover design in adult subjects (n=11). Mean serum fentanyl levels following these four doses of OTFC are shown in Figure 1. The curves for each dose level are similar in shape with increasing dose levels producing increasing serum fentanyl levels. Cmax and AUC0→∞ increased in a dose-dependent manner that is approximately proportional to the OTFC administered.

Figure 1. Mean Serum Fentanyl Concentration (ng/mL) in Adult Subjects Comparing 4 Doses of OTFC

The pharmacokinetic parameters of the four strengths of OTFC tested in the dose-proportionality study are shown in Table 3. The mean Cmax ranged from 0.39 - 2.51 ng/mL. The median time of maximum plasma concentration (Tmax) across these four doses of OTFC varied from 20 - 40 minutes (range of 20 - 480 minutes) as measured after the start of administration.

Table 3. Pharmacokinetic Parameters [Based on arterial blood samples.] in Adult Subjects Receiving 200, 400, 800, and 1600 mcg Units of OTFC
Pharmacokinetic Parameter | 200 mcg | 400 mcg | 800 mcg | 1600 mcg
Tmax, minute median (range) | 40 (20-120) | 25 (20-240) | 25 (20-120) | 20 (20-480)
Cmax, ng/mL mean (%CV) | 0.39 (23) | 0.75 (33) | 1.55 (30) | 2.51 (23)
AUC0-1440, ng/mL minute mean (%CV) | 102 (65) | 243 (67) | 573 (64) | 1026 (67)
t1/2, minute mean (%CV) | 193 (48) | 386 (115) | 381 (55) | 358 (45)

Distribution

Fentanyl is highly lipophilic. Animal data showed that following absorption, fentanyl is rapidly distributed to the brain, heart, lungs, kidneys and spleen followed by a slower redistribution to muscles and fat. The plasma protein binding of fentanyl is 80-85%. The main binding protein is alpha-1-acid glycoprotein, but both albumin and lipoproteins contribute to some extent. The free fraction of fentanyl increases with acidosis. The mean volume of distribution at steady state (Vss) was 4 L/kg.

Metabolism

Fentanyl is metabolized in the liver and in the intestinal mucosa to norfentanyl by cytochrome P450 3A4 isoform. Norfentanyl was not found to be pharmacologically active in animal studies [see Drug Interactions (7)].

Elimination

Fentanyl is primarily (more than 90%) eliminated by biotransformation to N-dealkylated and hydroxylated inactive metabolites. Less than 7% of the dose is excreted unchanged in the urine, and only about 1% is excreted unchanged in the feces. The metabolites are mainly excreted in the urine, while fecal excretion is less important. The total plasma clearance of fentanyl was 0.5 L/hr/kg (range 0.3 - 0.7 L/hr/kg). The terminal elimination half-life after OTFC administration is about 7 hours.

13. NONCLINICAL TOXICOLOGY

13.1 Carcinogenesis, Mutagenesis, Impairment of Fertility

Long-term studies in animals have not been performed to evaluate the carcinogenic potential of fentanyl.

Fentanyl citrate was not mutagenic in the in vitro Ames reverse mutation assay in S. typhimurium or E. coli, or the mouse lymphoma mutagenesis assay, and was not clastogenic in the in vivo mouse micronucleus assay.

Fentanyl has been shown to impair fertility in rats at doses of 30 mcg/kg IV and 160 mcg/kg subcutaneously. Conversion to the human equivalent doses indicates that this is within the range of the human recommended dosing for OTFC.

14. CLINICAL STUDIES

OTFC was investigated in clinical trials involving 257 opioid tolerant adult cancer patients experiencing breakthrough cancer pain. Breakthrough cancer pain was defined as a transient flare of moderate-to-severe pain occurring in cancer patients experiencing persistent cancer pain otherwise controlled with maintenance doses of opioid medications including at least 60 mg morphine/day, 50 mcg transdermal fentanyl/hour, or an equianalgesic dose of another opioid for a week or longer.

In two dose titration studies 95 of 127 patients (75%) who were on stable doses of either long-acting oral opioids or transdermal fentanyl for their persistent cancer pain titrated to a successful dose of OTFC to treat their breakthrough cancer pain within the dose range offered (200, 400, 600, 800, 1200 and 1600 mcg). A "successful" dose was defined as a dose where one unit of OTFC could be used consistently for at least two consecutive days to treat breakthrough cancer pain without unacceptable side effects. In these studies 11% of patients withdrew due to adverse reactions and 14% withdrew due to other reasons.

The successful dose of OTFC for breakthrough cancer pain was not predicted from the daily maintenance dose of opioid used to manage the persistent cancer pain and is thus best determined by dose titration.

A double-blind placebo controlled crossover study was performed in cancer patients to evaluate the effectiveness of OTFC for the treatment of breakthrough cancer pain. Of 130 patients who entered the study 92 patients (71%) achieved a successful dose during the titration phase. The distribution of successful doses is shown in Table 4.

Table 4. Successful Dose of OTFC Following Initial Titration
OTFC Dose | Total No. (%) (N=92)
200 mcg | 13 (14)
400 mcg | 19 (21)
600 mcg | 14 (15)
800 mcg | 18 (20)
1200 mcg | 13 (14)
1600 mcg | 15 (16)
Mean ±SD | 789±468 mcg

On average, patients over 65 years of age titrated to a mean dose that was about 200 mcg less than the mean dose to which younger adult patients were titrated.

OTFC was administered beginning at Time 0 minutes and produced more pain relief compared with placebo at 15, 30, 45, and 60 minutes as measured after the start of administration (see Figure 2). The differences were statistically significant.

Figure 2. Pain Relief (PR) Scores (Mean±SD) During the Double-Blind Phase - All Patients with Evaluable Episodes on Both OTFC and Placebo (N=86)

16. HOW SUPPLIED/STORAGE AND HANDLING

16.1 Storage and Handling

OTFC (oral transmucosal fentanyl citrate) is supplied in individually sealed child-resistant blister packages. The amount of fentanyl contained in OTFC can be fatal to a child. Patients and their caregivers must be instructed to keep OTFC out of the reach of children [see Boxed Warning - Warning: Importance Of Proper Patient Selection, Dosing, and Potential For Abuse, Warnings And Precautions (5), and Patient Counseling Information (17.1)].

Store at 20-25ºC (68-77ºF) with excursions permitted between 15° and 30°C (59° to 86°F) until ready to use. (See USP Controlled Room Temperature.) Protect OTFC from freezing and moisture. Do not use if the blister package has been opened.

16.2 Disposal of OTFC

Patients must be advised to dispose of any units remaining from a prescription as soon as they are no longer needed. While all units should be disposed of immediately after use, partially consumed units represent a special risk because they are no longer protected by the child resistant blister package, yet may contain enough medicine to be fatal to a child [see Patient Counseling Information (17.5)].

A temporary storage bottle is provided as part of the OTFC Child Safety Kit [see Patient Counseling Information (17.4)]. This container is to be used by patients or their caregivers in the event that a partially consumed unit cannot be disposed of promptly. Instructions for usage of this container are included in the Medication Guide.

Patients and members of their household must be advised to dispose of any units remaining from a prescription as soon as they are no longer needed. Instructions are included in Patient Counseling Information (17.6) and in the Medication Guide. If additional assistance is required, call Cephalon, Inc., at 1-800-896-5855.

16.3 How Supplied

OTFC is supplied in six dosage strengths. Each unit is individually wrapped in a child-resistant, protective blister package. These blister packages are packed 30 per shelf carton for use when patients have been titrated to the appropriate dose.

Each dosage unit has a white to off-white color. Each individual solid drug matrix is marked with "FENTANYL" and the strength of the unit ("200" ,"400", "600", "800" ,"1200", or "1600"). The dosage strength is also marked on the handle tag, the blister package and the carton. See blister package and carton for product information.

Dosage Strength (fentanyl base) | Carton/Blister Package Color | NDC Number
200 mcg | Gray | NDC 55253-070-30
400 mcg | Blue | NDC 55253-071-30
600 mcg | Orange | NDC 55253-072-30
800 mcg | Purple | NDC 55253-073-30
1200 mcg | Green | NDC 55253-074-30
1600 mcg | Burgundy | NDC 55253-075-30

Note: Colors are a secondary aid in product identification. Please be sure to confirm the printed dosage before dispensing.

17. PATIENT COUNSELING INFORMATION

See the Medication Guide for specific patient instructions.

17.1 Patient/Caregiver Instructions

1. Patients and their caregivers must be instructed that children exposed to OTFC are at high risk of FATAL RESPIRATORY DEPRESSION. Patients and their caregivers must be instructed to keep OTFC out of the reach of children [See How Supplied/Storage And Handling (16.1), Warnings And Precautions (5.2 and 5.3) and Medication Guide for specific patient instructions.]
2. Provide patients and their caregivers with a Medication Guide each time OTFC is dispensed because new information may be available
3. Instruct patients and their caregivers to keep both used and unused dosage units out of the reach of children. Partially consumed units represent a special risk to children. In the event that a unit is not completely consumed it must be properly disposed as soon as possible [see How Supplied/Storage And Handling (16.1), Warnings And Precautions (5.3), and Patient Counseling Information (17.5)]
4. Instruct patients not to take OTFC for acute pain, postoperative pain, pain from injuries, headache, migraine or any other short-term pain, even if they have taken other opioid analgesics for these conditions
5. Instruct patients on the meaning of opioid tolerance and that OTFC is only to be used as a supplemental pain medication for patients with pain requiring around-the-clock opioids, who have developed tolerance to the opioid medication, and who need additional opioid treatment of breakthrough pain episodes
6. Instruct patients that, if they are not taking an opioid medication on a scheduled basis (around-the-clock), they should not take OTFC
7. Instruct patients that, if the breakthrough pain episode is not relieved 15 minutes after finishing the OTFC unit, they may take ONLY ONE ADDITIONAL UNIT OF OTFC USING THE SAME STRENGTH FOR THAT EPISODE. Thus, patients should take no more than two units of OTFC for any breakthrough pain episode.
8. Instruct patients that they MUST wait at least 4 hours before treating another episode of breakthrough pain with OTFC
9. Instruct patients NOT to share OTFC and that sharing OTFC with anyone else could result in the other individual's death due to overdose
10. Make patients aware that OTFC contains fentanyl which is a strong pain medication similar to hydromorphone, methadone, morphine, oxycodone, and oxymorphone
11. Instruct patients that the active ingredient in OTFC, fentanyl, is a drug that some people abuse. OTFC should be taken only by the patient it was prescribed for, and it should be protected from theft or misuse in the work or home environment
12. Caution patients to talk to their doctor if breakthrough pain is not alleviated or worsens after taking OTFC
13. Instruct patients to use OTFC exactly as prescribed by their doctor and not to take OTFC more often than prescribed
14. Caution patients that OTFC can affect a person's ability to perform activities that require a high level of attention (such as driving or using heavy machinery). Warn patients taking OTFC of these dangers and counsel them accordingly
15. Warn patients to not combine OTFC with alcohol, sleep aids, or tranquilizers except by the orders of the prescribing physician, because dangerous additive effects may occur, resulting in serious injury or death
16. Inform female patients that if they become pregnant or plan to become pregnant during treatment with OTFC, they should ask their doctor about the effects that OTFC (or any medicine) may have on them and their unborn children

17.2 Dental Care

Because each OTFC unit contains approximately 2 grams of sugar (hydrated dextrates), frequent consumption may increase the risk of dental decay. The occurrence of dry mouth associated with the use of opioid medications (such as fentanyl) may add to this risk.

Post-marketing reports of dental decay have been received in patients taking OTFC [see Adverse Reactions (6.2)]. In some of these patients, dental decay occurred despite reported routine oral hygiene. As dental decay in cancer patients may be multi-factorial, patients using OTFC should consult their dentist to ensure appropriate oral hygiene.

17.3 Diabetic Patients

Advise diabetic patients that OTFC contains approximately 2 grams of sugar per unit.

17.4 OTFC Child Safety Kit

Provide patients and their caregivers with an OTFC Child Safety Kit, which contains educational materials and safe interim storage containers to help patients store OTFC and other medicines out of the reach of children. To obtain a supply of Child Safety Kits, health care professionals can call Cephalon, Inc., at 1-800-896-5855.

17.5 Disposal of Used OTFC Units

Patients must be instructed to dispose of completely used and partially used OTFC units.

1. After consumption of the unit is complete and the matrix is totally dissolved, throw away the handle in a trash container that is out of the reach of children.
2. If any of the drug matrix remains on the handle, place the handle under hot running tap water until all of the drug matrix is dissolved, and then dispose of the handle in a place that is out of the reach of children.
3. Dispose of handles in the child-resistant container (as described in steps 1 and 2) at least once a day.

If the patient does not entirely consume the unit and the remaining drug cannot be immediately dissolved under hot running water, the patient or caregiver must temporarily store the OTFC unit in the specially provided child-resistant container out of the reach of children until proper disposal is possible.

17.6 Disposal of Unopened OTFC Units When No Longer Needed

Patients and members of their household must be advised to dispose of any unopened units remaining from a prescription as soon as they are no longer needed.

To dispose of the unused OTFC units:

1. Remove the OTFC unit from its blister package using scissors, and hold the OTFC by its handle over the toilet bowl.
2. Using wire-cutting pliers cut off the drug matrix end so that it falls into the toilet.
3. Dispose of the handle in a place that is out of the reach of children.
4. Repeat steps 1, 2, and 3 for each OTFC unit. Flush the toilet twice after 5 units have been cut and deposited into the toilet.

Do not flush the entire OTFC units, OTFC handles, blister packages, or cartons down the toilet. Dispose of the handle where children cannot reach it [see How Supplied/Storage And Handling (16.1)].

Detailed instructions for the proper storage, administration, disposal, and important instructions for managing an overdose of OTFC are provided in the OTFC Medication Guide. Encourage patients to read this information in its entirety and giv then an opportunity to have their questions answered.

In the event that a caregiver requires additional assistance in disposing of excess unusable units that remain in the home after a patient has expired, instruct them to call the toll-free number for Cephalon, Inc., (1-800-896-5855) or seek assistance from their local DEA office.

MEDICATION GUIDE

Oral Transmucosal Fentanyl Citrate CII (OTFC) 200 mcg, 400 mcg, 600 mcg, 800 mcg, 1200 mcg, 1600 mcg

WARNING:

1. Do not use Oral Transmucosal Fentanyl Citrate (OTFC) unless you are regularly using other opioid pain medicines around-the-clock for your constant cancer pain and your body is used to these medicines.
2. You MUST keep OTFC in a safe place out of the reach of children. Accidental ingestion by a child is a medical emergency and can result in death. Death has been reported in children who have accidentally taken OTFC. If a child accidentally takes OTFC, get emergency help right away.

Read the Medication Guide that comes with Oral Transmucosal Fentanyl Citrate (OTFC) before you start taking it and each time you get a new prescription. There may be new information. This Medication Guide does not take the place of talking to your doctor about your medical condition or your treatment. Share this important information with members of your household.

What is the most important information I should know about Oral Transmucosal Fentanyl Citrate (OTFC)?

1. OTFC can cause life threatening breathing problems which can lead to death:
  - if you are not regularly using other opioid pain medicines around-the-clock for your constant cancer pain and your body is not used to these medicines. This means that you are not opioid tolerant.
  - if you do not use it exactly as prescribed by your doctor.
2. Your doctor will prescribe a starting dose of OTFC that is different than other fentanyl containing medicines you may have been taking. Do not substitute OTFC for other fentanyl medicines without talking with your doctor.
3. Use no more than 2 units of OTFC per episode of breakthrough cancer pain. You must wait at least 4 hours before using OTFC again for another episode of breakthrough cancer pain.

What is Oral Transmucosal Fentanyl Citrate (OTFC)?

- OTFC is a prescription medicine that contains the medicine fentanyl. OTFC is a federally controlled substance (CII) because it is a strong opioid pain medicine that can be abused by people who abuse prescription medicines or street drugs.
- OTFC is to be used only to treat breakthrough pain in adult patients with cancer (16 years of age and older) who are already using other opioid pain medicines for their constant (around-the-clock) cancer pain. OTFC is started only after you have been taking other opioid pain medicines and your body has gotten used to them (you are opioid tolerant). DO NOT USE OTFC if you are not opioid tolerant. Please talk with your doctor about whether or not you are opioid tolerant.
- You must stay under your doctor’s care while taking OTFC.
- OTFC must not be used for the treatment of short-term pain from injuries, surgery, or headaches, including migraines.
- Prevent theft and misuse. Keep OTFC in a safe place to protect it from being stolen since it can be a target for people who abuse narcotic medicines or street drugs.
- Never give OTFC to anyone else, even if they have the same symptoms you have. It may harm them and even cause death.
- Selling or giving away this medicine is against the law.

Who should not take Oral Transmucosal Fentanyl Citrate (OTFC)?

Do Not Take OTFC:

- if you are not already taking other opioid pain medicines around-the-clock for your constant cancer pain.
- for the treatment of short-term pain from injuries, surgery, or headaches, including migraines, or for pain that will go away in a few days, such as pain from doctor or dentist visits, or any short-lasting pain.
- if you are allergic to anything in OTFC. The active ingredient in OTFC is fentanyl. See the end of this Medication Guide for a complete list of ingredients in OTFC.

What should I tell my doctor before I start taking Oral Transmucosal Fentanyl Citrate (OTFC)?

Tell your doctor about all of your medical and mental problems, especially the ones listed below:

- Trouble breathing or lung problems such as asthma, wheezing, or shortness of breath
- A head injury or brain problem
- Liver or kidney problems
- Seizures (convulsions or fits)
- Slow heart rate or other heart problems
- Low blood pressure
- Mental problems including major depression or hallucinations (seeing or hearing things that are not there)
- A past or present drinking problem or alcoholism, or a family history of this problem
- A past or present drug abuse or addiction problem, or a family history of this problem
- If you are diabetic. Each OTFC unit contains about ½ teaspoon (2 grams) of sugar.

Tell your doctor if you are:

- pregnant or planning to become pregnant. OTFC may harm your unborn baby.
- breast feeding. Fentanyl passes through your breast milk and it can cause serious harm to your baby. You should not use OTFC while breast feeding.

Tell your doctor about all the medicines you take, including prescription and non-prescription medicines, vitamins, and herbal and dietary supplements. Some medicines may cause serious or life-threatening medical problems when taken with OTFC. Sometimes, the doses of certain medicines and OTFC need to be changed if used together.

Do not take any medicine while using OTFC until you have talked to your doctor. Your doctor will tell you if it is safe to take other medicines while you are using OTFC. Be especially careful about other medicines that make you sleepy such as other pain medicines, anti-depressant medicines, sleeping pills, anxiety medicines, antihistamines, or tranquilizers.

Know the medicines you take. Keep a list of them to show your doctor and pharmacist.

How should I use Oral Transmucosal Fentanyl Citrate (OTFC)?

- Use OTFC exactly as prescribed by your doctor. Do not take OTFC more often than prescribed. Talk to your doctor about your pain. Your doctor can decide if your dose of OTFC needs to be changed.
- Each unit of OTFC is sealed in its own blister package.
- Do not open the blister package until you are ready to use OTFC.
- When you are ready to use OTFC, cut open the package using scissors and remove the OTFC unit. The end of the unit marked with "FENTANYL" and the strength of the unit ("200", "400", "600", "800", "1200", or "1600") is the end that is to be placed in your mouth as described below.
- Place OTFC in your mouth between your cheeks and gums and actively suck on the medicine.
- Move OTFC around in your mouth, especially along your cheeks.
- Twirl the handle often.
- Finish the OTFC unit completely in 15 minutes to get the most relief. If you finish OTFC too quickly, you will swallow more of the medicine and get less relief.
- Do not bite or chew OTFC. You will get less relief for your breakthrough pain.
- You may drink some water before using OTFC but you should not drink or eat anything while using OTFC.
- If you begin to feel dizzy, sick to your stomach, or very sleepy before OTFC is completely dissolved, remove OTFC from your mouth. Dispose of OTFC right away or put it in the temporary storage bottle in the Child Safety Kit for later disposal.
- Use 1 unit of OTFC for an episode of breakthrough cancer pain. Consume the unit over 15 minutes.
- If your breakthrough cancer pain is not relieved 15 minutes after you finished the OTFC unit, use ONLY 1 more dose of OTFC at this time.
- Wait at least 4 more hours before using OTFC again for another episode of breakthrough cancer pain.
- Remember, you must continue taking your regularly-used around-the-clock opioid medicine while taking OTFC.
- Limit the use of OTFC to four or fewer units per day.
- Talk to your doctor if your dose of OTFC does not relieve your breakthrough cancer pain. Your doctor will decide if your dose of OTFC needs to be changed.
- Talk to your doctor if you have more than 4 episodes of breakthrough cancer pain per day. The dose of your around-the-clock opioid pain medicine may need to be adjusted.
- If you take too much OTFC or overdose, call 911 or your local emergency number for help.

How should I dispose of Oral Transmucosal Fentanyl Citrate (OTFC) after use?

Partially used OTFC units may contain enough medicine to be harmful or fatal to a child or other adults who have not been prescribed OTFC. You must properly dispose of the OTFC handle right away after use even if there is little or no medicine left on it. Please follow these directions to dispose of the handle:

1. Once you have finished the OTFC unit and the medicine is totally gone, throw the handle away in a place that is out of the reach of children.
2. If any medicine remains on the handle after you have finished, place the handle under hot running water until the medicine is gone, and then throw the handle away out of the reach of children and pets.
3. If you did not finish the entire OTFC unit and you cannot dissolve the medicine under hot running water right away, put the OTFC in the temporary storage bottle that you received in the OTFC Child Safety Kit for safe keeping. Push the OTFC unit into the opening on the top until it falls completely into the bottle. Never leave unused or partially used OTFC units where children or pets can get to them.
4. Dispose of the handles in the temporary storage bottle as soon as you can by following the directions in steps 1 and 2. You must dispose of all handles in the temporary storage bottle at least once a day.

Do not flush entire unused OTFC units, OTFC handles, or blister packages down the toilet.

What should I avoid while taking Oral Transmucosal Fentanyl Citrate (OTFC)?

- Do not drive, operate heavy machinery, or do other dangerous activities until you know how OTFC affects how alert you are. OTFC can make you sleepy. Ask your doctor when it is okay to do these activities.
- Do not drink alcohol while using OTFC. It can increase your chance of getting dangerous side effects.
- Do not take any medicine while using OTFC until you have talked to your doctor. Your doctor will tell you if it is safe to take other medicines while you are using OTFC. Be especially careful about medicines that make you sleepy such as other pain medicines, anti-depressant medicines, sleeping pills, anxiety medicines, antihistamines, or tranquilizers.

What are the possible or reasonably likely SIDE EFFECTS of Oral Transmucosal Fentanyl Citrate (OTFC)?

- OTFC can cause serious breathing problems that can become life-threatening, especially if used the wrong way. See “What is the most important information I should know about OFTC?"
- Call your doctor or get emergency medical help right away if you:
  - have trouble breathing
  - have extreme drowsiness with slowed breathing
  - have slow shallow breathing (little chest movement with breathing)
  - feel faint, very dizzy, confused, or have unusual symptoms

These can be symptoms that you have taken too much (overdose) OTFC or the dose is too high for you. These symptoms may lead to serious problems or death if not treated right away. Do not take another dose of OTFC.

- OTFC can cause your blood pressure to drop. This can make you feel dizzy if you get up too fast from sitting or lying down.
- OTFC can cause physical dependence. Do not stop taking OTFC or any other opioid without talking to your doctor. You could become sick with uncomfortable withdrawal symptoms because your body has become used to these medicines. Physical dependency is not the same as drug addiction.
- There is a chance of abuse or addiction with OTFC. The chance is higher if you are or have been addicted to or abused other medications, street drugs, or alcohol, or if you have a history of mental problems.

The most common side effects of OTFC are nausea, vomiting, dizziness and sleepiness. Other side effects include headache, low energy and constipation. Constipation (not often enough or hard bowel movements) is a very common side effect of pain medicines (opioids) including OTFC and is unlikely to go away without treatment. Talk to your doctor about dietary changes, and the use of laxatives (medicines to treat constipation) and stool softeners to prevent or treat constipation while taking OTFC.

OTFC contains sugar. Cavities and tooth decay have occurred in patients taking OTFC. When taking OTFC, you should talk to your dentist about proper care of your teeth.

Talk to your doctor about any side effects that bother you or that do not go away.

These are not all the possible side effects of OTFC. For a complete list, ask your doctor.Call your doctor for medical advice about side effects.

You may report side effects to FDA at 1-800-FDA-1088.

How should I store Oral Transmucosal Fentanyl Citrate (OTFC)?

- Keep OTFC in a safe place away from children. Accidental use by a child is a medical emergency and can result in death. If a child accidentally takes OTFC, get emergency help right away.
- OTFC is supplied in single sealed child-resistant blister packages. Store OTFC at room temperature, 59° to 86°F (15° to 30°C) until ready to use.
- Always keep OTFC in a secure place to protect from theft.

How should I dispose of unopened Oral Transmucosal Fentanyl Citrate (OTFC) units when they are no longer needed?

- Dispose of any unopened OTFC units remaining from a prescription as soon as they are no longer needed.
- If you are no longer using OTFC or if you have unused OTFC in your home, please follow these steps to dispose of the OTFC as soon as possible.
  1. Remove all OTFC from the locked storage space.
  2. Remove one OTFC unit from its blister package using scissors, and hold the OTFC by its handle over the toilet bowl.
  3. Using wire-cutting pliers, cut the medicine end off so that it falls into the toilet.
  4. Throw the handle away in a place that is out of the reach of children.
  5. Repeat steps 2, 3, and 4 for each OTFC.
  6. Flush the toilet twice after 5 OTFC units have been cut. Do not flush more than 5 OTFC units at a time.
  - Do not flush entire unused OTFC units, OTFC handles, or blister packages down the toilet.

If you need help with disposal of OTFC, call Cephalon, Inc., at 1-800-896-5855.

General Information About the Safe and Effective Use of Oral Transmucosal Fentanyl Citrate (OTFC)

Medicines are sometimes prescribed for purposes other than those listed in a Medication Guide. Use OTFC only for the purpose for which it was prescribed.

Do not give OTFC to other people, even if they have the same symptoms you have.

OTFC can harm other people and even cause death.

Sharing OTFC is against the law

This Medication Guide summarizes the most important information about OTFC. If you would like more information, talk with your doctor. You can also ask your pharmacist or doctor for information about OTFC that is written for healthcare professionals. You can also call Cephalon, Inc., at 1-800-896-5855.

What are the ingredients of Oral Transmucosal Fentanyl Citrate (OTFC)?

Active Ingredient: fentanyl citrate.

Inactive Ingredients: Sugar, citric acid, dibasic sodium phosphate, artificial berry flavor, magnesium stearate, modified food starch, and confectioner's sugar.

How do I use the Oral Transmucosal Fentanyl Citrate (OTFC) Child Safety Kit?

- You can use the OTFC Child Safety Kit to help you store OTFC and your other medicines out of the reach of children. It is very important that you use the items in the OTFC Child Safety Kit to protect the children in your home.
- If you were not offered a Child Safety Kit when you received your medicine, call Cephalon, Inc., at 1-800-896-5855 to request one.

The OTFC Child Safety Kit contains important information on the safe storage and handling of OTFC. The kit contents include:

- A child-resistant lock for you to secure the storage space where you keep OTFC and any other medicines at home.
- A portable locking pouch for you to keep a small supply of OTFC nearby for your immediate use. The rest of your OTFC must be kept in the locked storage space.
  - Keep this pouch secured with its lock and keep it out of the reach and sight of children.

- A child-resistant temporary storage bottle.
- If for some reason you cannot finish the entire OTFC unit and cannot immediately dissolve the medicine under hot tap water, immediately put the OTFC unit in the temporary storage bottle for safe keeping.
  - Push the OTFC unit into the opening on the top until it falls completely into the bottle. You must properly dispose of the OTFC unit as soon as you can.
- See “How should I dispose of unopened OTFC units when they are no longer needed?” for proper disposal of OTFC.

This Medication Guide has been approved by the U.S. Food and Drug Administration.

Rx Only

Manufactured by:
Anesta Corp., Salt Lake City, UT 84116, USA

Reference Number: 00010677.05

Printed in USA

Repacked by:
H.J. Harkins Company, Inc., Nipomo, CA 93444, USA